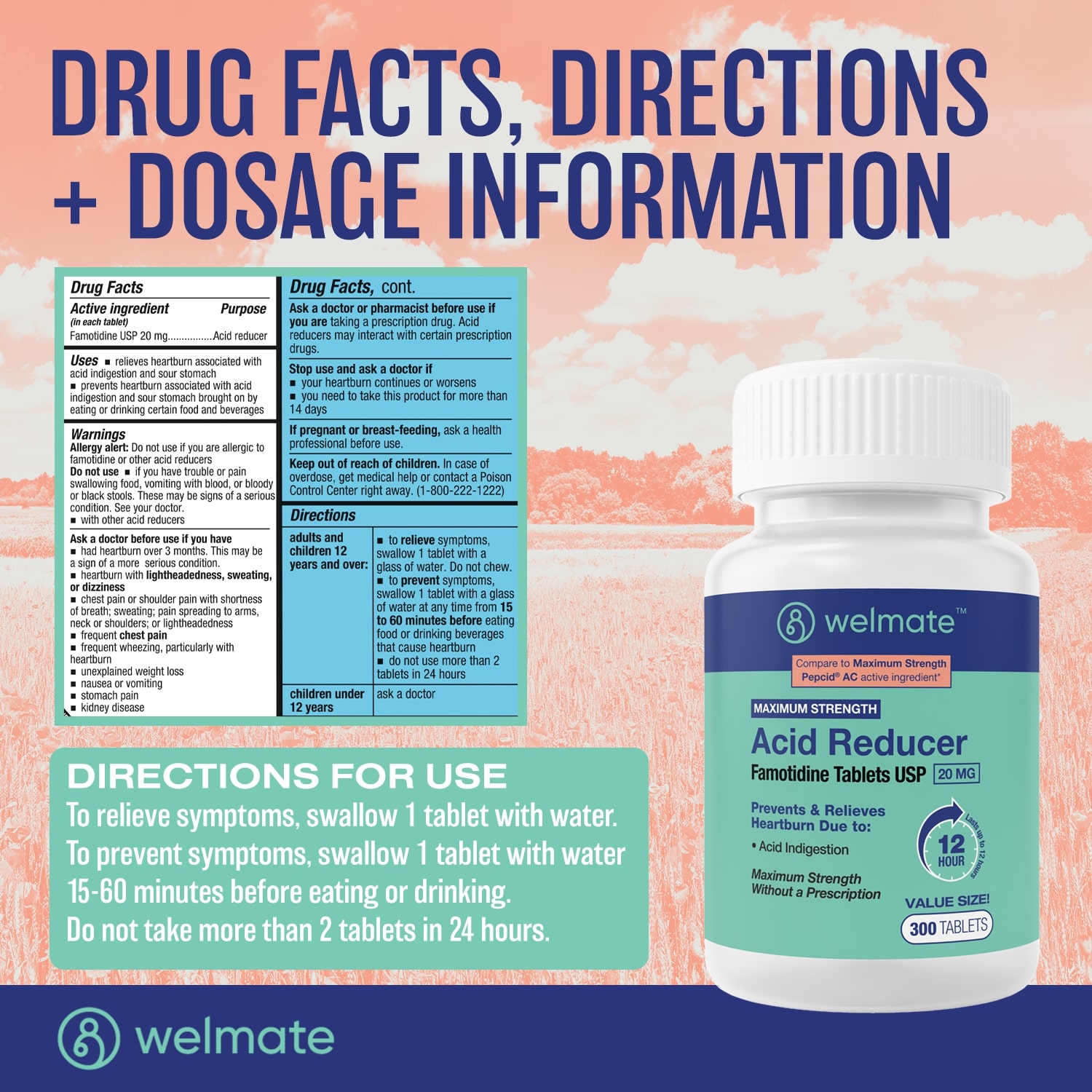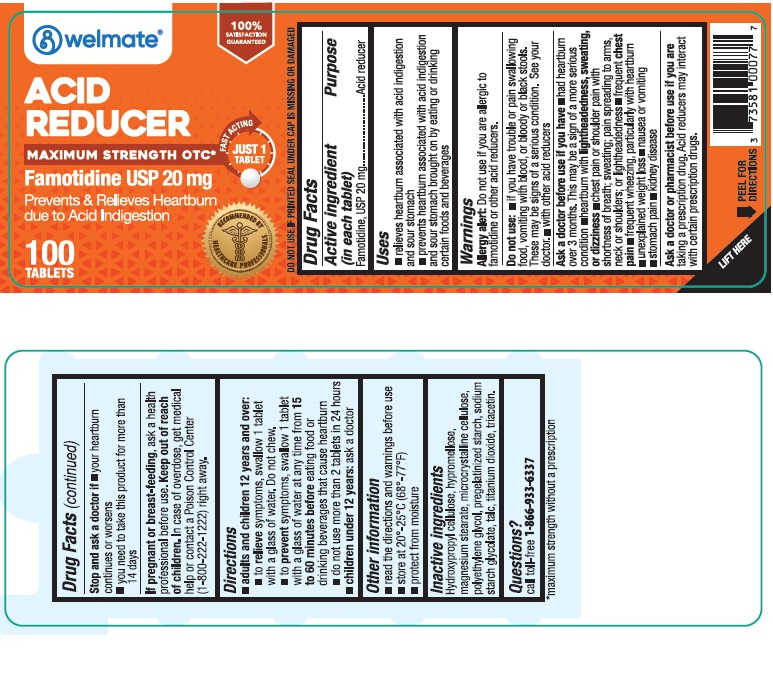 DRUG LABEL: Welmate Famotidine 20mg
NDC: 73581-109 | Form: TABLET
Manufacturer: YYBA Corp
Category: otc | Type: HUMAN OTC DRUG LABEL
Date: 20250729

ACTIVE INGREDIENTS: FAMOTIDINE 20 mg/1 1
INACTIVE INGREDIENTS: HYDROXYPROPYL CELLULOSE, UNSPECIFIED; TRIACETIN; TALC; SODIUM STARCH GLYCOLATE TYPE A CORN; TITANIUM DIOXIDE; MICROCRYSTALLINE CELLULOSE; HYPROMELLOSES; MAGNESIUM STEARATE; POLYETHYLENE GLYCOL, UNSPECIFIED; STARCH, CORN

Welmate Famotidine 20mg 73581-109

Active ingredient (in each tablet)

Famotidine, USP 20 mg

Purpose

Acid reducer

Uses

- relieves heartburn associated with acid indigestion and sour stomach
- prevents heartburn associated with acid indigestion and sour stomach brought on by eating or drinking certain food and beverages

Warnings

Allergy alert
Do not use if you are allergic to famotidine or other acid reducers

Do not use

- if you have trouble or pain swallowing food, vomiting with blood, or bloody or black stools. These may be signs of a serious condition. See your doctor.
- with other acid reducers

Ask a doctor before use if you have

- had heartburn over 3 months. This may be a sign of a more serious condition.
- heartburn with lightheadedness, sweating, or dizziness
- chest pain or shoulder pain with shortness of breath; sweating; pain spreading to arms, neck or shoulders; or lightheadedness
- frequent chest pain
- frequent wheezing, particularly with heartburn
- unexplained weight loss
- nausea or vomiting
- stomach pain
- kidney disease

Ask a doctor or pharmacist before use if you aretaking a prescription drug. Acid reducers may interact with certain prescription drugs.

Stop use and ask a doctor if

- your heartburn continues or worsens
- you need to take this product for more than 14 days

Keep out of reach of children.

In case of overdose, get medical help or contact a Poison Control Center right away (1-800-222-1222).

If pregnant or breast-feeding

ask a health professional before use.

Directions

adults and children 12 years and over:

- to relieve symptoms, swallow 1 tablet with a glass of water. Do not chew.
- to prevent symptoms, swallow 1 tablet (of 10 mg) with a glass of water at any time from 15 to 60 minutes before eating food or drinking beverages that cause heartburn
- to prevent symptoms, swallow 1 tablet (of 20 mg) with a glass of water at any time from 10 to 60 minutes before eating food or drinking beverages that cause heartburn
- before eating food or drinking beverages that cause heartburn
- do not use more than 2 tablets in 24 hours

children under 12 years:

- ask a doctor

Inactive Ingredients

Microcrystalline Cellulose, Pre-gelatinized Starch, Sodium Starch Glycolate, Hydroxypropyl Cellulose, Magnesium Stearate, Hypromellose, Titanium Dioxide, Triacetin, Talc, Macrogol

Other information

- read the directions and warnings before use
- keep the carton. It contains important information.
- store at 20°C to 25°C (68°F to 77°F)
- protect from moisture